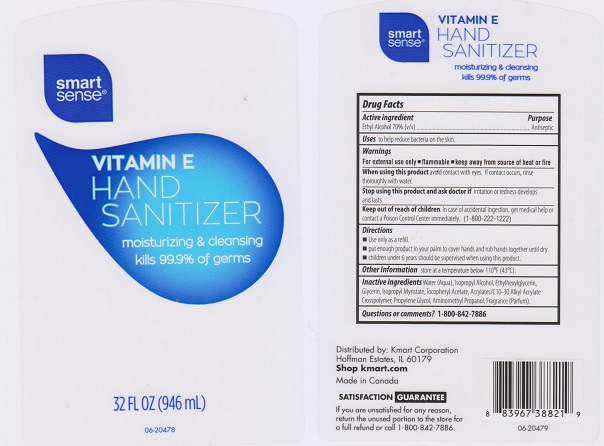 DRUG LABEL: SMART SENSE
NDC: 49738-478 | Form: LIQUID
Manufacturer: KMART CORPORATION
Category: otc | Type: HUMAN OTC DRUG LABEL
Date: 20160309

ACTIVE INGREDIENTS: ALCOHOL 700 mg/1 mL
INACTIVE INGREDIENTS: WATER; ISOPROPYL ALCOHOL; ETHYLHEXYLGLYCERIN; GLYCERIN; ISOPROPYL MYRISTATE; .ALPHA.-TOCOPHEROL ACETATE; CARBOMER COPOLYMER TYPE A (ALLYL PENTAERYTHRITOL CROSSLINKED); PROPYLENE GLYCOL; AMINOMETHYLPROPANOL

DRUG FACTS

Active ingredient

Ethyl Alcohol 70% v/v

Purpose

Antiseptic

Uses

to help reduce bacteria on the skin.

Warnings

For external use only.

- flammable
- keep away from source of heat or fire

When using this product

avoid contact with eyes. If contact occurs, rinse thoroughly with water.

Stop using this product and ask doctor if

irritation or redness develops and lasts.

Keep out of reach of children.

In case of accidental ingestion, get medical help or contact a Poison Control Center immediately (1-800-222-1222)

Directions

- Use only as a refill.
- put enough product in your palm to cover hands and rub hands together until dry.
- children under 6 years should be supervised when using this product.

Other information

store at temperature below 110F (43C).

Inactive ingredients

Water (Aqua), Isopropyl Alcohol, Ethylhexylglycerin, Glycerin, Isopropyl Myristate, Tocopheryl Acetate, Acrylates/C10-30 Alkyl Acrylate Crosspolymer, Propylene Glycol, Aminomethyl Propanol, Fragrance (Parfum).

Questions or comments?

1-800-842-7886